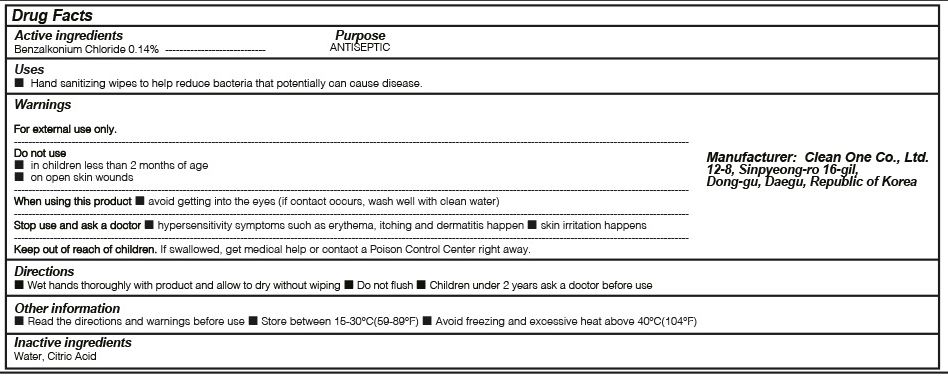 DRUG LABEL: Clean Disinfectant Wipes
NDC: 78506-001 | Form: LIQUID
Manufacturer: Clean One Co., Ltd.
Category: otc | Type: HUMAN OTC DRUG LABEL
Date: 20200908

ACTIVE INGREDIENTS: BENZALKONIUM CHLORIDE 0.0054 g/3.6 g
INACTIVE INGREDIENTS: WATER; CITRIC ACID MONOHYDRATE

Drug Facts

ACTIVE INGREDIENT

Benzalkonium Chloride

INACTIVE INGREDIENTS

Water, Citric Acid

PURPOSE

Antiseptic

WARNINGS

For external use only.
--------------------------------------------------------------------------------------------------------
Do not use
■ in children less than 2 months of age
■ on open skin wounds
--------------------------------------------------------------------------------------------------------
When using this product
■ avoid getting into the eyes (if contact occurs, wash well with clean water)
--------------------------------------------------------------------------------------------------------
Stop use and ask a doctor
■ hypersensitivity symptoms such as erythema, itching and dermatitis happen
■ skin irritation happens

KEEP OUT OF REACH OF CHILDREN

If swallowed, get medical help or contact a Poison Control Center right away.

Uses

Hand sanitizing wipes to help reduce bacteria that potentially can cause disease.

Directions

■ Wet hands thoroughly with product and allow to dry without wiping
■ Do not flush
■ Children under 2 years ask a doctor before use

Other information

■ Read the directions and warnings before use
■ Store between 15-30℃(59-89℉)
■ Avoid freezing and excessive heat above 40℃(104 ℉)